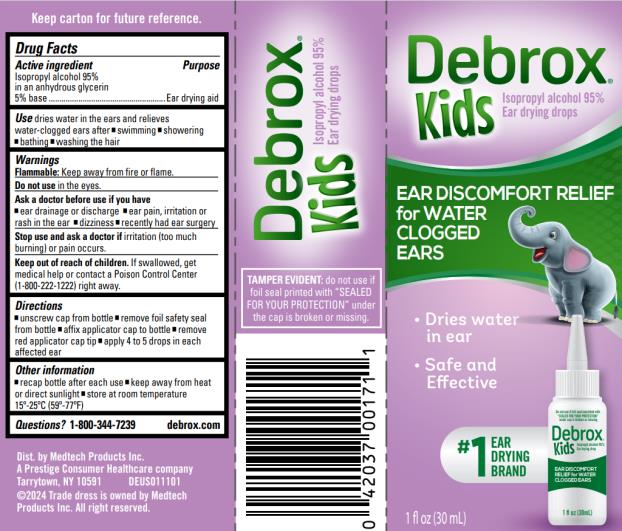 DRUG LABEL: Debrox Kids
NDC: 63029-325 | Form: LIQUID
Manufacturer: Medtech Products Inc.
Category: otc | Type: HUMAN OTC DRUG LABEL
Date: 20240509

ACTIVE INGREDIENTS: ISOPROPYL ALCOHOL 95 mL/100 mL
INACTIVE INGREDIENTS: GLYCERIN

Debrox Kids Ear Discomfort Relief 63029-325

Drug Facts

Purpose

Isopropyl alcohol 95% in an anhydrous glycerin 5% base ....Ear drying aid

Use

dries water in the ears and relieves water-clogged ears after

- swimming
- showering
- bathing
- washing the hair

Warnings

Flammable: Keep away from fire or flame

Ask a doctor before use if you have

• ear drainage or discharge

• ear pain, irritation or rash in the ear • dizziness

• recently had ear surgery

Keep out of reach of children.

If swallowed, get medical help or contact a Poison

Control Center (1-800-222-1222) right away.

Directions

- unscrew cap from bottle
- remove foil safety seal from bottle
- affix applicator cap to bottle
- remove red applicator cap tip
- apply 4 to 5 drops in each affected ear

Other information

- recap bottle after each use
- keep away from heat or direct sunlight
- store at room temperature 15-25ºC (59-77ºF)

Inactive

Glycerin

Questions?

1-800-344-7239 debrox.com

PRINCIPAL DISPLAY PANEL

Debrox ® Kids

Isopropyl alcohol 95%

Ear Drying Drops

1 FL OZ (30 mL)